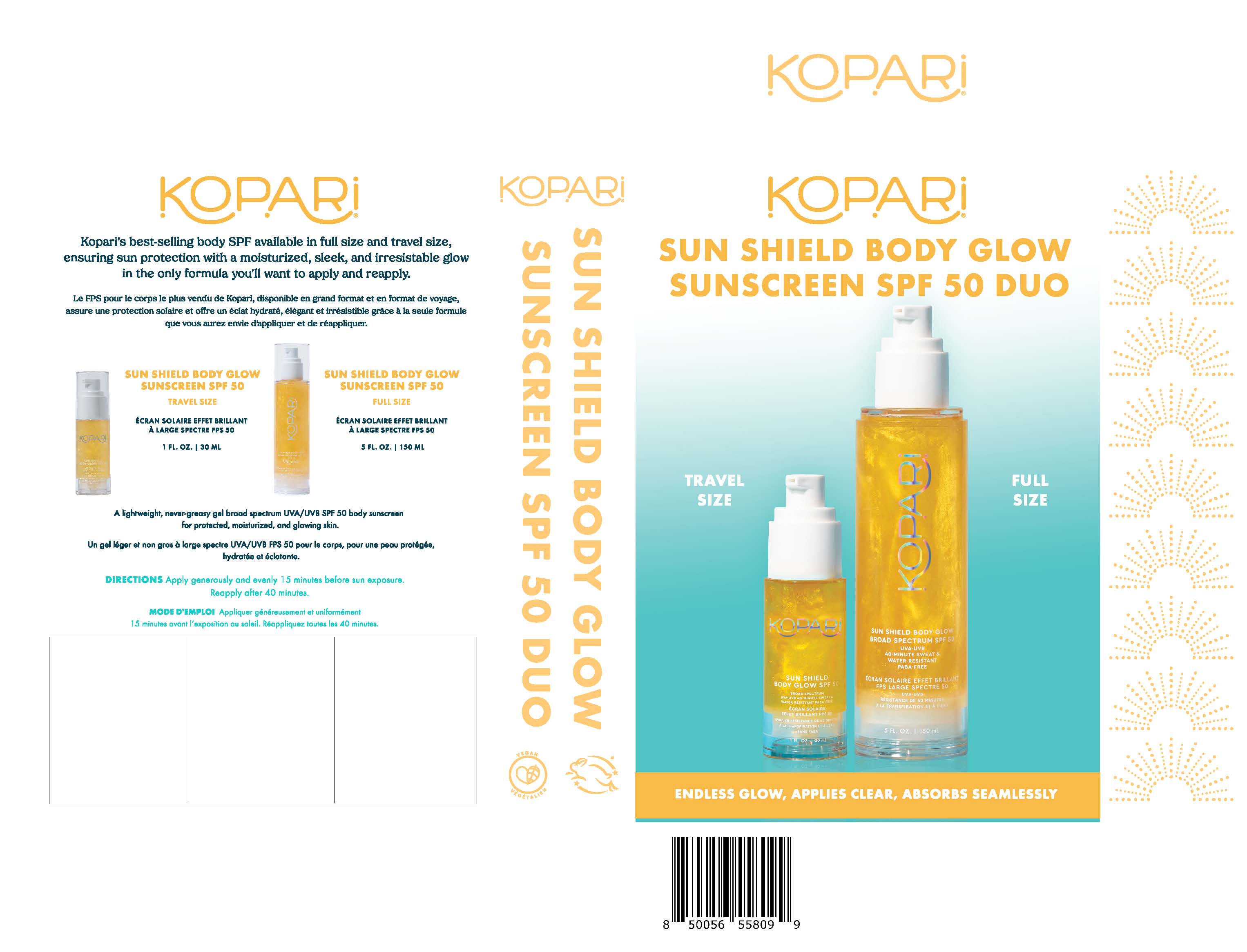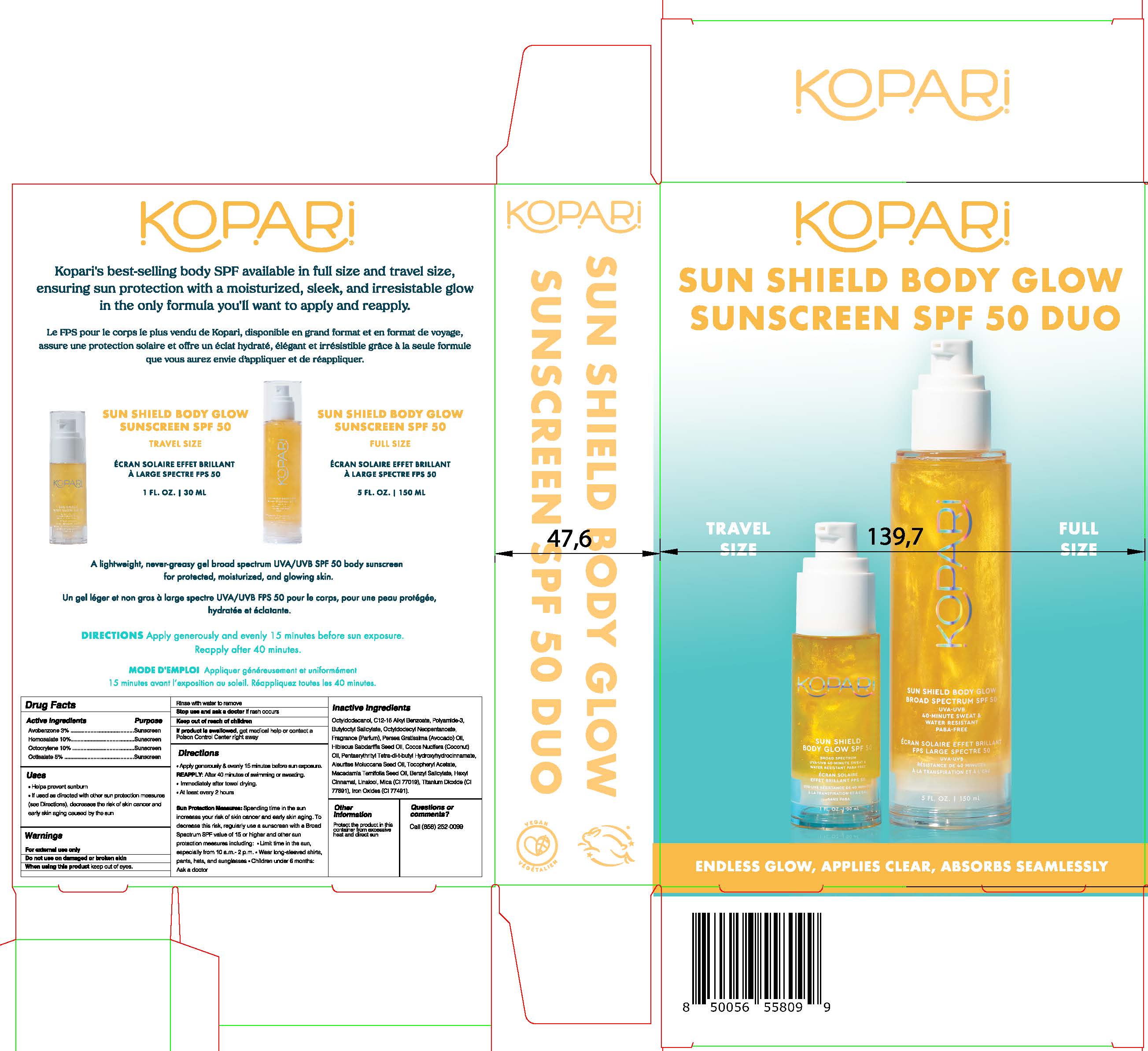 DRUG LABEL: Sun Essentials SPF Duo Kit
NDC: 84130-008 | Form: KIT | Route: TOPICAL
Manufacturer: Koco Life LLC
Category: otc | Type: HUMAN OTC DRUG LABEL
Date: 20240628

ACTIVE INGREDIENTS: OCTOCRYLENE 100 mg/1 mL; HOMOSALATE 100 mg/1 mL; OCTISALATE 50 mg/1 mL; AVOBENZONE 30 mg/1 mL; OCTOCRYLENE 100 mg/1 mL; HOMOSALATE 100 mg/1 mL; OCTISALATE 50 mg/1 mL; AVOBENZONE 30 mg/1 mL
INACTIVE INGREDIENTS: BENZYL SALICYLATE; OCTYLDODECYL NEOPENTANOATE; MICA; OCTYLDODECANOL; COCONUT OIL; TITANIUM DIOXIDE; ALKYL (C12-15) BENZOATE; BUTYLOCTYL SALICYLATE; AVOCADO OIL; MACADAMIA OIL; LINALOOL, (+)-; FERRIC OXIDE RED; PENTAERYTHRITOL TETRAKIS(3-(3,5-DI-TERT-BUTYL-4-HYDROXYPHENYL)PROPIONATE); KUKUI NUT OIL; .ALPHA.-TOCOPHEROL ACETATE; .ALPHA.-HEXYLCINNAMALDEHYDE; POLYAMIDE-3 (12000 MW); HIBISCUS SABDARIFFA SEED OIL; BENZYL SALICYLATE; OCTYLDODECYL NEOPENTANOATE; MICA; OCTYLDODECANOL; COCONUT OIL; TITANIUM DIOXIDE; ALKYL (C12-15) BENZOATE; BUTYLOCTYL SALICYLATE; AVOCADO OIL; MACADAMIA OIL; LINALOOL, (+)-; FERRIC OXIDE RED; PENTAERYTHRITOL TETRAKIS(3-(3,5-DI-TERT-BUTYL-4-HYDROXYPHENYL)PROPIONATE); KUKUI NUT OIL; .ALPHA.-TOCOPHEROL ACETATE; .ALPHA.-HEXYLCINNAMALDEHYDE; POLYAMIDE-3 (12000 MW); HIBISCUS SABDARIFFA SEED OIL

Sun Essentials SPF Duo Kit

Active ingredients

Avobenzone 3%

Homosalate 10%

Octocrylene 10%

Octisalate 5%

Purpose

Avobenzone 3%.....................Sunscreen

Homosalate 10%....................Sunscreen

Octocrylene 10%....................Sunscreen

Octisalate 5%.........................Sunscreen

Uses

• Helps prevent sunburn

• If used as directed with other sunprotection measures (see Directions),decreases the risk of skin cancer and earlyskin aging caused by the sun

Warnings

For e xternal use only

Do not use on damaged or broken skin

When using this product keep out of eyes
Rinse with water to remove

Stop use and ask a doctor if rash occurs

Keep out of reach of children
If product is swallowed, get medical help or contact a Poison Control Center right away

Directions

• Apply generously & evenly 15 minutesbefore sun exposure.

REAPPLY: After 40 minutes of swimming or sweating. • Immediately after towel drying.• At least every 2 hours

Sun Protection Measures: Spending time in the sun increases your risk of skin cancer and early skin aging. To decrease this risk, regularly use a sunscreen with a Broad Spectrum SPF value of 15 or higher and other sun protection measures including: • Limit time in the sun, especially from 10 a.m.- 2 p.m. • Wear long-sleeved shirts, pants, hats, and sunglasses • Children under 6 months: Ask a doctor

Inactive ingredients

Octyldodecanol, C12-15 Alkyl Benzoate, Polyamide-3, Butyloctyl Salicylate, Octyldodecyl Neopentanoate, Fragrance (Parfum), Persea Gratissima (Avocado) Oil, Hibiscus Sabdariffa Seed Oil, Cocos Nucifera (Coconut) Oil, Pentaerythrityl Tetra-di-t-butyl Hydroxyhydrocinnamate, Aleurites Moluccana Seed Oil, Tocopheryl Acetate, Macadamia Ternifolia Seed Oil, Benzyl Salicylate, Hexyl Cinnamal, Linalool, Mica (CI 77019), Titanium Dioxide (CI 77891), Iron Oxides (CI 77491).

Other information

Protect the product in this container from excessive heat and direct sun

Questions or comments?

Call (858) 252-0099

PACKAGE LABEL

Kopari

Sun Shield Body Glow

Sunscreen SPF 50 DUO

Endless Glow, Applies Clear, Absorbs Seamlessly